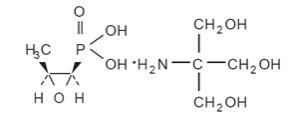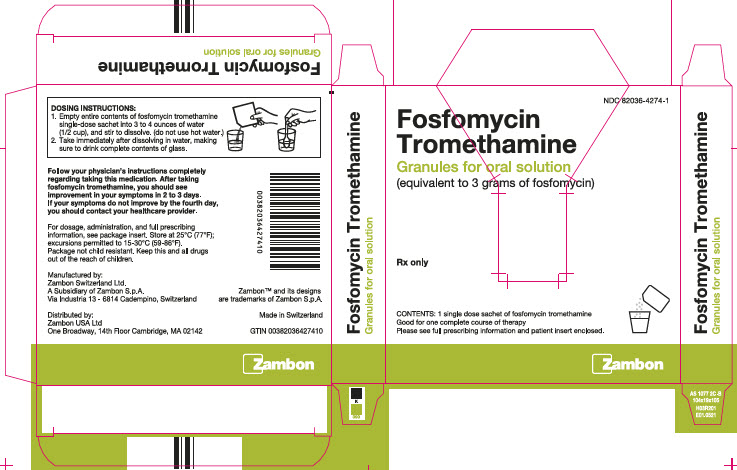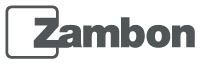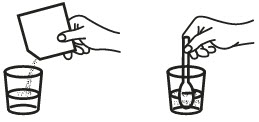 DRUG LABEL: Fosfomycin Tromethamine
NDC: 82036-4274 | Form: POWDER
Manufacturer: Zambon USA, Ltd
Category: prescription | Type: HUMAN PRESCRIPTION DRUG LABEL
Date: 20231003

ACTIVE INGREDIENTS: FOSFOMYCIN TROMETHAMINE 3 g/1 1
INACTIVE INGREDIENTS: TANGERINE; ORANGE; SACCHARIN; SUCROSE

Fosfomycin Tromethamine
Granules for Oral Solution
Rx only

DESCRIPTION

Fosfomycin tromethamine granules for oral solution contains fosfomycin tromethamine, a synthetic, broad spectrum, bactericidal antibiotic for oral administration. It is available as a single-dose sachet which contains white granules consisting of 5.631 grams of fosfomycin tromethamine (equivalent to 3 grams of fosfomycin), and the following inactive ingredients: mandarin flavor, orange flavor, saccharin, and sucrose. The contents of the sachet must be dissolved in water. Fosfomycin tromethamine, a phosphonic acid derivative, is available as (1 R,2 S)-(1,2-epoxypropyl)phosphonic acid, compound with 2-amino-2-(hydroxymethyl)-1,3-propanediol (1:1). It is a white granular compound with a molecular weight of 259.2. Its empirical formula is C3H7O4P•C4H11NO3, and its chemical structure is as follows:

CLINICAL PHARMACOLOGY

Absorption: Fosfomycin tromethamine is rapidly absorbed following oral administration and converted to the free acid, fosfomycin. Absolute oral bioavailability under fasting conditions is 37%. After a single 3-gram dose of fosfomycin tromethamine, the mean (± 1 SD) maximum serum concentration (Cmax) achieved was 26.1 (± 9.1) mcg/mL within 2 hours. The oral bioavailability of fosfomycin is reduced to 30% under fed conditions. Following a single 3-gram oral dose of fosfomycin tromethamine with a high-fat meal, the mean Cmax achieved was 17.6 (± 4.4) mcg/mL within 4 hours.

Cimetidine does not affect the pharmacokinetics of fosfomycin when coadministered with fosfomycin tromethamine. Metoclopramide lowers the serum concentrations and urinary excretion of fosfomycin when coadministered with fosfomycin tromethamine. (See PRECAUTIONS, Drug Interactions.)

Distribution: The mean apparent steady-state volume of distribution (Vss) is 136.1 (±44.1) L following oral administration of fosfomycin tromethamine. Fosfomycin is not bound to plasma proteins.

Fosfomycin is distributed to the kidneys, bladder wall, prostate, and seminal vesicles. Following a 50 mg/kg dose of fosfomycin to patients undergoing urological surgery for bladder carcinoma, the mean concentration of fosfomycin in the bladder, taken at a distance from the neoplastic site, was 18.0 mcg per gram of tissue at 3 hours after dosing. Fosfomycin has been shown to cross the placental barrier in animals and man.

Excretion: Fosfomycin is excreted unchanged in both urine and feces. Following oral administration of fosfomycin tromethamine, the mean total body clearance (CLTB) and mean renal clearance (CLR) of fosfomycin were 16.9 (± 3.5) L/hr and 6.3 (± 1.7) L/hr, respectively. Approximately 38% of a 3-gram dose of fosfomycin tromethamine is recovered from urine, and 18% is recovered from feces. Following intravenous administration, the mean CLTB and mean CLR of fosfomycin were 6.1 (±1.0) L/hr and 5.5 (± 1.2) L/hr, respectively.

A mean urine fosfomycin concentration of 706 (± 466) mcg/mL was attained within 2-4 hours after a single oral 3-gm dose of fosfomycin tromethamine under fasting conditions. The mean urinary concentration of fosfomycin was 10 mcg/mL in samples collected 72-84 hours following a single oral dose of fosfomycin tromethamine.

Following a 3-gram dose of fosfomycin tromethamine administered with a high fat meal, a mean urine fosfomycin concentration of 537 (± 252) mcg/mL was attained within 6-8 hours. Although the rate of urinary excretion of fosfomycin was reduced under fed conditions, the cumulative amount of fosfomycin excreted in the urine was the same, 1118 (± 201) mg (fed) vs. 1140 mg (± 238) (fasting). Further, urinary concentrations equal to or greater than 100 mcg/mL were maintained for the same duration, 26 hours, indicating that fosfomycin tromethamine can be taken without regard to food.

Following oral administration of fosfomycin tromethamine, the mean half-life for elimination (t1/2) is 5.7 (± 2.8) hours.

Special Populations:

Geriatric: Based on limited data regarding 24-hour urinary drug concentrations, no differences in urinary excretion of fosfomycin have been observed in elderly subjects. No dosage adjustment is necessary in the elderly.

Gender: There are no gender differences in the pharmacokinetics of fosfomycin.

Renal Insufficiency: In 5 anuric patients undergoing hemodialysis, the t1/2 of fosfomycin during hemodialysis was 40 hours. In patients with varying degrees of renal impairment (creatinine clearances varying from 54 mL/min to 7 mL/min), the t1/2 of fosfomycin increased from 11 hours to 50 hours. The percent of fosfomycin recovered in urine decreased from 32% to 11% indicating that renal impairment significantly decreases the excretion of fosfomycin.

Microbiology

Fosfomycin (the active component of fosfomycin tromethamine) has in vitro activity against a broad range of gram-positive and gram-negative aerobic microorganisms which are associated with uncomplicated urinary tract infections. Fosfomycin is bactericidal in urine at therapeutic doses. The bactericidal action of fosfomycin is due to its inactivation of the enzyme enolpyruvyl transferase, thereby irreversibly blocking the condensation of uridine diphosphate-N-acetylglucosamine with p-enolpyruvate, one of the first steps in bacterial cell wall synthesis. It also reduces adherence of bacteria to uroepithelial cells.

There is generally no cross-resistance between fosfomycin and other classes of antibacterial agents such as beta-lactams and aminoglycosides.

Fosfomycin has been shown to be active against most strains of the following microorganisms, both in vitro and in clinical infections as described in the INDICATIONS AND USAGE section:

Aerobic gram-positive microorganisms
Enterococcus faecalis

Aerobic gram-negative microorganisms
Escherichia coli

The following in vitro data are available, but theirclinical significance is unknown.

Fosfomycin exhibits in vitro minimum inhibitory concentrations (MIC’s) of 64 mcg/mL or less against most (≥ 90%) strains of the following microorganisms; however, the safety and effectiveness of fosfomycin in treating clinical infections due to these microorganisms has not been established in adequate and well-controlled clinical trials:

Aerobic gram-positive microorganisms
Enterococcus faecium

Aerobic gram-negative microorganisms
Citrobacter diversus
Citrobacter freundii
Enterobacter aerogenes
Klebsiella oxytoca
Klebsiella pneuomoniae
Proteus mirabilis
Proteus vulgaris
Serratia marcescens

SUSCEPTIBILITY TESTING

Dilution Techniques:

Quantitative methods are used to determine minimum inhibitory concentrations (MIC’s). These MIC’s provide estimates of the susceptibility of bacteria to antimicrobial compounds. One such standardized procedure uses a standardized agar dilution method^1 or equivalent with standardized inoculum concentrations and standardized concentrations of fosfomycin tromethamine (in terms of fosfomycin base content) powder supplemented with 25 mcg/mL of glucose-6-phosphate. BROTH DILUTION METHODS SHOULDNOT BE USED TO TEST SUSCEPTIBILITY TO FOSFOMYCIN. The MIC values obtained should be interpreted according to the following criteria:

MIC (mcg/mL) | Interpretation
≤ 64 | Susceptible (S)
128 | Intermediate (I)
≥ 256 | Resistant (R)

A report of “susceptible” indicates that the pathogen is likely to be inhibited by usually achievable concentrations of the antimicrobial compound in the urine. A report of “intermediate” indicates that the result should be considered equivocal, and, if the microorganism is not fully susceptible to alternative, clinically feasible drugs, the test should be repeated. This category provides a buffer zone that prevents small uncontrolled technical factors from causing major discrepancies in interpretation. A report of “resistant” indicates that usually achievable concentrations of the antimicrobial compound in the urine are unlikely to be inhibitory and that other therapy should be selected.

Standardized susceptibility test procedures require the use of laboratory control microorganisms. Standard fosfomycin tromethamine powder should provide the following MIC values for agar dilution testing in media containing 25 mcg/mL of glucose-6-phosphate. [Broth dilution testing should not be performed].

Microorganism | MIC (mcg/mL)
Enterococcus faecalis ATCC 29212 | 32-128
Escherichia coli ATCC 25922 | 0.5-2
Pseudomonas aeruginosa ATCC 27853 | 2-8
Staphylococcus aureus ATCC 29213 | 0.5-4

Diffusion Techniques:

Quantitative methods that require measurement of zone diameters also provide reproducible estimates of the susceptibility of bacteria to antimicrobial agents. One such standardized procedure^2 requires the use of standardized inoculum concentrations. This procedure uses paper disks impregnated with 200-mcg fosfomycin and 50-mcg of glucose-6-phosphate to test the susceptibility of microorganisms to fosfomycin.

Reports from the laboratory providing results of the standard single-disk susceptibility tests with disks containing 200-mcg of fosfomycin and 50-mcg of glucose-6-phosphate should be interpreted according to the following criteria:

Zone Diameter (mm) | Interpretation
≥ 16 | Susceptible (S)
13-15 | Intermediate (I)
≤ 12 | Resistant (R)

Interpretation should be stated as above for results using dilution techniques. Interpretation involves correlation of the diameter obtained in the disk test with the MIC for fosfomycin.

As with standardized dilution techniques, diffusion methods require use of laboratory control microorganisms that are used to control the technical aspects of the laboratory procedures. For the diffusion technique, the 200-mcg fosfomycin disk with the 50-mcg of glucose-6-phosphate should provide the following zone diameters in these laboratory quality control strains:

Microorganism | Zone Diameter (mm)
Escherichia coli ATCC 25922 | 22-30
Staphylococcus aureus ATCC 25923 | 25-33

INDICATIONS AND USAGE

Fosfomycin tromethamine is indicated only for the treatment of uncomplicated urinary tract infections (acute cystitis) in women due to susceptible strains of Escherichia coli and Enterococcus faecalis. Fosfomycin tromethamine is not indicated for the treatment of pyelonephritis or perinephric abscess.

If persistence or reappearance of bacteriuria occurs after treatment with fosfomycin tromethamine, other therapeutic agents should be selected. (See PRECAUTIONS and CLINICAL STUDIES sections.)

CONTRAINDICATIONS

Fosfomycin tromethamine is contraindicated in patients with known hypersensitivity to the drug.

WARNINGS

Clostridium difficile associated diarrhea (CDAD) has been reported with use of nearly all antibacterial agents, including fosfomycin tromethamine, and may range in severity from mild diarrhea to fatal colitis. Treatment with antibacterial agents alters the normal flora of the colon leading to overgrowth of C. difficile.

C. difficile produces toxins A and B which contribute to the development of CDAD. Hypertoxin producing strains of C. difficile cause increased morbidity and mortality, as these infections can be refractory to antimicrobial therapy and may require colectomy. CDAD must be considered in all patients who present with diarrhea following antibiotic use. Careful medical history is necessary since CDAD has been reported to occur over two months after the administration of antibacterial agents.

If CDAD is suspected or confirmed, ongoing antibiotic use not directed against C. difficile may need to be discontinued. Appropriate fluid and electrolyte management, protein supplementation, antibiotic treatment of C. difficile, and surgical evaluation should be instituted as clinically indicated.

PRECAUTIONS

General

Do not use more than one single dose of fosfomycin tromethamine to treat a single episode of acute cystitis. Repeated daily doses of fosfomycin tromethamine did not improve the clinical success or microbiological eradication rates compared to single dose therapy, but did increase the incidence of adverse events. Urine specimens for culture and susceptibility testing should be obtained before and after completion of therapy.

Information for Patients

Patients should be informed:

- That fosfomycin tromethamine can be taken with or without food.
- That their symptoms should improve in two to three days after taking fosfomycin tromethamine; if not improved, the patient should contact her health care provider.
- Diarrhea is a common problem caused by antibiotics which usually ends when the antibiotic is discontinued. Sometimes after starting treatment with antibiotics, patients can develop watery and bloody stools (with or without stomach cramps and fever) even as late as two or more months after having taken the last dose of the antibiotic. If this occurs, patients should contact their physician as soon as possible.

Drug Interactions

Metoclopramide: When coadministered with fosfomycin tromethamine, metoclopramide, a drug which increases gastrointestinal motility, lowers the serum concentration and urinary excretion of fosfomycin. Other drugs that increase gastrointestinal motility may produce similar effects.

Cimetidine: Cimetidine does not affect the pharmacokinetics of fosfomycin when coadministered with fosfomycin tromethamine.

Carcinogenesis, Mutagenesis, Impairment of Fertility

Long term carcinogenicity studies in rodents have not been conducted because fosfomycin tromethamine is intended for single dose treatment in humans. Fosfomycin tromethamine was not mutagenic or genotoxic in the in vitro Ames’ bacterial reversion test, in cultured human lymphocytes, in Chinese hamster V79 cells, and the in vivo mouse micronucleus assay. Fosfomycin tromethamine did not affect fertility or reproductive performance in male and female rats.

Pregnancy:

Teratogenic Effects

When administered intramuscularly as the sodium salt at a dose of 1 gram to pregnant women, fosfomycin crosses the placental barrier. Fosfomycin tromethamine crosses the placental barrier of rats; it does not produce teratogenic effects in pregnant rats at dosages as high as 1000 mg/kg/day (approximately 9 and 1.4 times the human dose based on body weight and mg/m^2, respectively). When administered to pregnant female rabbits at dosages as high as 1000 mg/kg/day (approximately 9 and 2.7 times the human dose based on body weight and mg/m^2, respectively), fetotoxicities were observed. However, these toxicities were seen at maternally toxic doses and were considered to be due to the sensitivity of the rabbit to changes in the intestinal microflora resulting from the antibiotic administration. There are, however, no adequate and well-controlled studies in pregnant women. Because animal reproduction studies are not always predictive of human response, this drug should be used during pregnancy only if clearly needed.

Nursing Mothers

It is not known whether fosfomycin tromethamine is excreted in human milk. Because many drugs are excreted in human milk and because of the potential for serious adverse reactions in nursing infants from fosfomycin tromethamine, a decision should be made whether to discontinue nursing or to not administer the drug, taking into account the importance of the drug to the mother.

Pediatric Use

Safety and effectiveness in children age 12 years and under have not been established in adequate and well-controlled studies.

Geriatric Use

Clinical studies of fosfomycin tromethamine did not include sufficient numbers of subjects aged 65 and over to determine whether they respond differently from younger subjects. Other reported clinical experience has not identified differences in responses between the elderly and younger patients. In general, dose selection for an elderly patient should be cautious, usually starting at the low end of the dosing range, reflecting the greater frequency of decreased hepatic, renal, or cardiac function, and of concomitant disease or other drug therapy.

ADVERSE REACTIONS

Clinical Trials:

In clinical studies, drug related adverse events which were reported in greater than 1% of the fosfomycin-treated study population are listed below:

Drug-Related Adverse Events (%) in Fosfomycin and Comparator Populations
Adverse Events | Fosfomycin N=1233 | Nitrofurantoin N=374 | Trimethoprim/ sulfamethoxazole N=428 | Ciprofoxacin N=455
Diarrhea | 9.0 | 6.4 | 2.3 | 3.1
Vaginitis | 5.5 | 5.3 | 4.7 | 6.3
Nausea | 4.1 | 7.2 | 8.6 | 3.4
Headache | 3.9 | 5.9 | 5.4 | 3.4
Dizziness | 1.3 | 1.9 | 2.3 | 2.2
Asthenia | 1.1 | 0.3 | 0.5 | 0.0
Dyspepsia | 1.1 | 2.1 | 0.7 | 1.1

In clinical trials, the most frequently reported adverse events occurring in > 1% of the study population regardless of drug relationship were: diarrhea 10.4%, headache 10.3%, vaginitis 7.6%, nausea 5.2%, rhinitis 4.5%, back pain 3.0%, dysmenorrheal 2.6%, pharyngitis 2.5%, dizziness 2.3%, abdominal pain 2.2%, pain 2.2%, dyspepsia 1.8%, asthenia 1.7%, and rash 1.4%.

The following adverse events occurred in clinical trials at a rate of less than 1%, regardless of drug relationship: abnormal stools, anorexia, constipation, dry mouth, dysuria, ear disorder, fever, flatulence, flu syndrome, hematuria, infection, insomnia, lymphadenopathy, menstrual disorder, migraine, myalgia, nervousness, paresthesia, pruritus, SGPT increased, skin disorder, somnolence, and vomiting.

One patient developed unilateral optic neuritis, an event considered possibly related to fosfomycin tromethamine therapy.

Post-marketing Experience:

Serious adverse events from the marketing experience with fosfomycin tromethamine outside of the United States have been rarely reported and include: angioedema, aplastic anemia, asthma (exacerbation), cholestatic jaundice, hepatic necrosis, and toxic megacolon.

Although causality has not been established, during post marketing surveillance, the following events have occurred in patients prescribed fosfomycin tromethamine: anaphylaxis and hearing loss.

Laboratory Changes:

Significant laboratory changes reported in U.S. clinical trials of fosfomycin tromethamine without regard to drug relationship include: increased eosinophil count, increased or decreased WBC count, increased bilirubin, increased SGPT, increased SGOT, increased alkaline phosphatase, decreased hematocrit, decreased hemoglobin, increased and decreased platelet count. The changes were generally transient and were not clinically significant.

OVERDOSAGE

In acute toxicology studies, oral administration of high doses of fosfomycin tromethamine up to 5 g/kg were well-tolerated in mice and rats, produced transient and minor incidences of watery stools in rabbits, and produced diarrhea with anorexia in dogs occurring 2-3 days after single dose administration. These doses represent 50-125 times the human therapeutic dose.

The following events have been observed in patients who have taken fosfomycin tromethamine in overdose: vestibular loss, impaired hearing, metallic taste, and general decline in taste perception. In the event of overdosage, treatment should be symptomatic and supportive.

DOSAGE AND ADMINISTRATION

The recommended dosage for women 18 years of age and older for uncomplicated urinary tract infection (acute cystitis) is one sachet of fosfomycin tromethamine. Fosfomycin tromethamine may be taken with or without food.

Fosfomycin tromethamine should not be taken in its dry form. Always mix fosfomycin tromethamine with water before ingesting. (See PREPARATION section.)

PREPARATION

Fosfomycin tromethamine should be taken orally. Pour the entire contents of a single-dose sachet of fosfomycin tromethamine into 3 to 4 ounces of water (1/2 cup) and stir to dissolve. Do not use hot water. Fosfomycin tromethamine should be taken immediately after dissolving in water.

HOW SUPPLIED

Fosfomycin tromethamine granules for oral solution is available as a single-dose sachet containing the equivalent of 3 grams of fosfomycin.

NDC

Single-dose sachet 82036-4274-8

One unit carton 82036-4274-1

Store at 25°C (77°F); excursions permitted to 15-30°C (59-86°F).

Keep this and all drugs out of the reach of children.

CLINICAL STUDIES

In controlled, double-blind studies of acute cystitis performed in the United States, a single-dose of fosfomycin tromethamine was compared to three other oral antibiotics (See table below). The study population consisted of patients with symptoms and signs of acute

cystitis of less than 4 days duration, no manifestations of upper tract infection (e.g., flank pain, chills, fever), no history of recurrent urinary tract infections (20% of patients in the clinical studies had a prior episode of acute cystitis within the preceding year), no known structural abnormalities, no clinical or laboratory evidence of hepatic dysfunction, and no known or suspected CNS disorders, such as epilepsy, or other factors which would predispose to seizures. In these studies, the following clinical success (resolution of symptoms) and microbiologic eradication rates were obtained.

Treatment Arm | Treatment Duration (days) | Microbiologic Eradication Rate |  | Clinical Success Rate | Outcome (based on difference in microbiologic eradication rates 5-11 days post therapy)
 |  | 5-11 days post therapy | Study day 12-21
Fosfomycin | 1 | 630/771 (82%) | 591/771 (77%) | 542/771 (70%)
Ciprofloxacin | 7 | 219/222 (98%) | 219/222 (98%) | 213/222 (96%) | Fosfomycin inferior to ciprofloxacin
Trimethoprim/ sulfamethoxazole | 10 | 194/197 (98%) | 194/197 (98%) | 186/197 (94%) | Fosfomycin inferior to trimethoprim/ sulfamethoxazole
Nitrofurantoin | 7 | 180/238 (76%) | 180/238 (76%) | 183/238 (77%) | Fosfomycin equivalent to nitrofurantoin

Pathogen | Fosfomycin 3 gram singledose | Ciprofloxacin 250 mg bid x 7 days | Trimethoprim/ sulfamethoxazole 160 mg/800 mg bid x 10 days | Nitrofurantoin 100 mg bid x 7 days
E. coli | 509/644 (79%) | 184/187 (98%) | 171/174 (98%) | 146/187 (78%)
E. faecalis | 10/10 (100%) | 0/0 | 4/4 (100%) | 1/2 (50%)

REFERENCES

1. National Committee for Clinical Laboratory Standards, Methods for Dilution. Antimicrobial Susceptibility Tests for Bacteria that Grow Aerobically – Third Edition; Approved Standard NCCLS Document M7-A3, Vol. 13, No. 25 NCCLS, Villanova, PA, December, 1993.

2. National Committee for Clinical Laboratory Standards, Performance Standard for Antimicrobial Disk Susceptibility Tests – Fifth Edition; Approved Standard NCCLS Document M2-A5, Vol. 13, No. 24 NCCLS, Villanova, PA, December, 1993.

Manufactured by:
Zambon Switzerland Ltd.
A Subsidiary of Zambon S.p.A.

Via Industria 13
6814 Cadempino, Switzerland

Made in Switzerland

Distributed by:
Zambon USA Ltd.

One Broadway, 14th Floor, Cambridge MA 02142

ZambonTM and its designs are trademarks of Zambon S.p.A.

Rev. June 2021

PATIENT COUNSELING INFORMATION

Fosfomycin Tromethamine

Granules for oral solution

(equivalent to 3 grams of fosfomycin)

Information for patients
After taking fosfomycin tromethamine

granules for oral solution
you should see improvement in your symptoms

in 2 to 3 days.

If your symptoms do not improve by the fourth day,
you should contact your healthcare professional.

2

This booklet provides information on fosfomycin tromethamine granules for oral solution, the medication your doctor has prescribed for your bladder infection (acute cystitis), as well as background on the infection itself. It is important to know that, although your therapy is completed when you take the single dose of fosfomycin tromethamine granules for oral solution, it may take 2 to 3 days for symptoms to improve. If your symptoms do not improve by the fourth day, you should contact your healthcare professional.

3

What is fosfomycin tromethamine granules for oral solution for?

Fosfomycin tromethamine granules for oral solution is for the treatment of acute cystitis in women. Acute cystitis, also known as bladder infection, is a type of uncomplicated urinary tract infection. Acute cystitis is caused by bacteria entering your bladder (which is normally bacteria free) resulting in irritation to your bladder lining. Fosfomycin tromethamine granules for oral solution is a bladder-specific antibiotic prescribed to kill the bacteria causing your infection. As the bacteria die, your bladder lining begins to heal.

4

How does fosfomycin tromethamine granules for oral solution work?

Fosfomycin tromethamine granules for oral solution starts working to kill bacteria within hours after taking it. Although you only take fosfomycin tromethamine granules for oral solution once, fosfomycin tromethamine granules for oral solution is designed to stay in your bladder for more than 3 days, continuing to kill the bacteria. Therefore, after taking fosfomycin tromethamine granules for oral solution, you should see improvement in your symptoms in 2 to 3 days. If your symptoms do not improve by the fourth day, you should contact your healthcare professional.

5

What is in the sachet (packet)?

The sachet packet contains white granules of fosfomycin tromethamine granules for oral solution (fosfomycin tromethamine), an antibiotic, along with a small amount of sweetener (saccharin and sucrose) and orange and mandarin flavoring.

6

Can I take fosfomycin tromethamine granules for oral solution if I am pregnant or breast-feeding?

Adequate and well-controlled studies involving the use of fosfomycin tromethamine granules for oral solution in pregnant and breast-feeding women have not been conducted. If your physician feels it is clearly needed, fosfomycin tromethamine granules for oral solution can be taken. Please inform your healthcare provider if you know you are pregnant or are breast-feeding.

7

How do I take fosfomycin tromethamine granules for oral solution?

1. Empty entire contents of fosfomycin tromethamine granules for oral solution sachet into 3 to 4 ounces of water (½ cup), and stir to dissolve. Do not use hot water.

2. Take immediately after dissolving in water, making sure to drink complete contents of glass.

8

Is this all I need to do?

Yes. One sachet of fosfomycin tromethamine granules for oral solution is a complete therapy for treating your bladder infection. The medicine in fosfomycin tromethamine granules for oral solution goes directly to your bladder and stays there for several days to kill the bacteria causing your infection.

9

Does fosfomycin tromethamine granules for oral solution always work?

No antibiotic works 100% of the time. In controlled clinical trials, using strict criteria for evaluation, approximately three quarters of patients were cured after single dose treatment with fosfomycin tromethamine granules for oral solution. This cure rate was equivalent to that for patients treated with Macrobid®**, and somewhat lower than for patients treated with Cipro®† and with Bactrim®††.

10

Will I experience side effects?

Because fosfomycin tromethamine granules for oral solution goes right to the site of your infection, side effects from the drug are uncommon. Less than 1 patient in 10 (9.0%) taking fosfomycin tromethamine granules for oral solution may experience diarrhea. Other infrequently seen side effects are vaginitis (5.5%), nausea (4.1%), headache (3.9%), dizziness (1.3%), tiredness (1.1%), and indigestion (1.1%).

11

What if I am allergic to fosfomycin tromethamine granules for oral solution?

Fosfomycin tromethamine granules for oral solution is not related to penicillin or other antibiotics that commonly cause allergic reactions. If you have a history of allergy to antibiotics, you should be able to take fosfomycin tromethamine granules for oral solution on your doctor’s advice.

12

What about taking fosfomycin tromethamine granules for oral solution with other drugs?

Fosfomycin tromethamine granules for oral solution has very few interactions with other drugs. If you are currently taking a gastrointestinal drug called Reglan®* (metoclopramide hydrochloride), you should not take fosfomycin tromethamine granules for oral solution unless you have discussed this with your doctor.

13

Some other precautions:

Do not take this or any other medication if it was prescribed for someone else.

KEEP FOSFOMYCIN TROMETHAMINE GRANULES FOR ORAL SOLUTION OUT OF THE REACH OF CHILDREN.

Do not use after the expiration date printed on the box.

*Reglan is a registered trademark of A. H. Robins Company.
**Macrobid is a registered trademark of Procter & Gamble.
†Cipro is a registered trademark of Bayer Corporation.
††Bactrim is a registered trademark of Roche Pharmaceuticals.

14

What is acute cystitis?

Acute cystitis is the common name for uncomplicated urinary tract infection. It is an infection of the urinary bladder that causes the bladder lining to become inflamed or irritated.

15

What causes acute cystitis?

Acute cystitis is usually caused by bacteria that enter the bladder. Bacteria can travel from the anal area to collect in the vagina and then enter the urethra to finally reach the bladder.

16

What are the usual symptoms?

Typical symptoms include frequent urination, painful urination, and a bladder that never feels totally empty. Other symptoms include pain in the pubic area.

17

Is acute cystitis dangerous?

Normally it is not, unless the bacteria in the urine causing it have traveled upward to infect the kidneys. Your doctor has prescribed fosfomycin tromethamine granules for oral solution to prevent this from occurring.

18

How is acute cystitis diagnosed and treated?

Acute cystitis is diagnosed on the basis of your symptoms and/or a urine culture to identify the responsible bacteria. It is most often treated with antibiotics.

19

Is there something I can take to relieve my pain?

There are medications available in addition to your primary therapy, fosfomycin tromethamine granules for oral solution, that your healthcare provider can recommend. Talk to your healthcare provider about additional medication.

20

Is there anything I can do to avoid acute cystitis?

Bladder infections that occur repeatedly in women are often associated with sexual activity and/or certain methods of contraception. Urinating immediately and completely after intercourse can help flush out bacteria that may have been accidentally forced into the urethra. Women who use a diaphragm with spermicidal jelly or use spermicidal foam with a condom should consider another form of contraception if they continue to experience infections.

21

You should also wipe from front to back to avoid contaminating the urethral entrance with bacteria from the bowels. You should discuss these and other ways to prevent bladder infections with your healthcare provider.

22

DO NOT TAKE THIS OR ANY MEDICATION IF IT WAS PRESCRIBED FOR SOMEONE ELSE.

FOSFOMYCIN TROMETHAMINE GRANULES FOR ORAL SOLUTION IS NOT RECOMMENDED FOR PATIENTS UNDER 18 YEARS OF AGE.

KEEP FOSFOMYCIN TROMETHAMINE GRANULES FOR ORAL SOLUTION OUT OF REACH OF CHILDREN.

DO NOT USE AFTER EXPIRATION DATE.

Manufactured by:
Zambon Switzerland Ltd.
A Subsidiary of Zambon S.p.A.
Via Industria 13
6814 Cadempino, Switzerland

Distributed by:

Zambon USA Ltd.
One Broadway, 14th Floor, Cambridge MA 02142

ZambonTM and its designs are trademarks of Zambon S.p.A.

Made in Switzerland

Zambon USA Ltd.

06/2021

PRINCIPAL DISPLAY PANEL

NDC 82036-4274-1
Fosfomycin Tromethamine
Granules for oral solution
(equivalent to 3 grams of fosfomycin)

Rx only
CONTENTS: 1 single dose of fosfomycin tromethamine
Good for one complete course of therapy